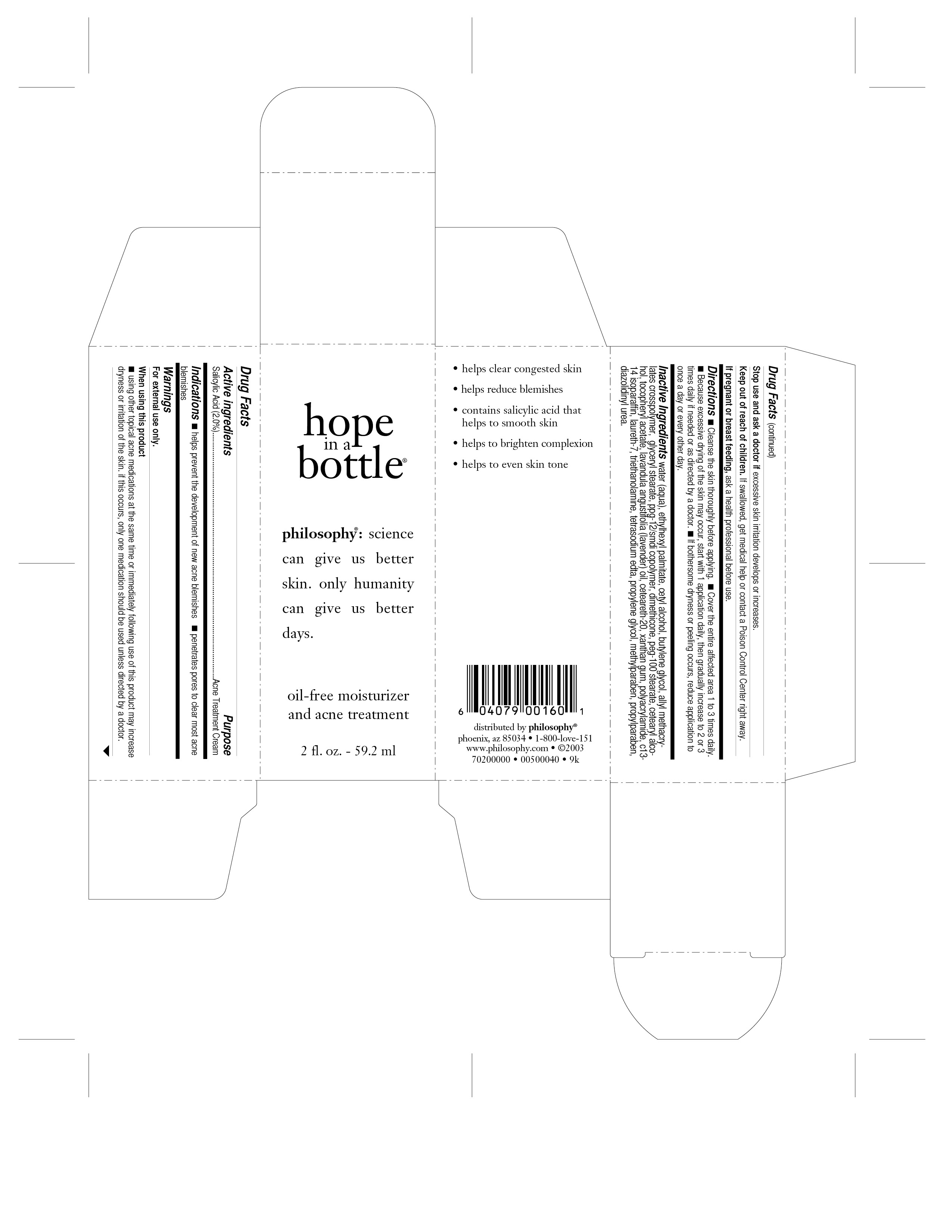 DRUG LABEL: Hope In A Bottle
NDC: 50184-2900 | Form: LOTION
Manufacturer: Philosophy, Inc.
Category: otc | Type: HUMAN OTC DRUG LABEL
Date: 20110928

ACTIVE INGREDIENTS: SALICYLIC ACID 1.184 mL/59.2 mL
INACTIVE INGREDIENTS: WATER; ETHYLHEXYL PALMITATE; CETYL ALCOHOL; BUTYLENE GLYCOL; GLYCERYL MONOSTEARATE; DIMETHICONE; CETOSTEARYL ALCOHOL; ALPHA-TOCOPHEROL ACETATE; LAVENDER OIL; PEG-100 STEARATE; POLYOXYL 20 CETOSTEARYL ETHER; XANTHAN GUM; C13-14 ISOPARAFFIN; LAURETH-7; TROLAMINE; EDETATE SODIUM; PROPYLENE GLYCOL; METHYLPARABEN; PROPYLPARABEN; DIAZOLIDINYL UREA

OTC DRUG FACTS

ACTIVE INGREDIENT

SALICYLIC ACID 2%

INACTIVE INGREDIENT

water

ethylhexyl palmitate

cetyl alcohol

butylene glycol
glyceryl stearate
allyl methacrylates crosspolymer
ppg-12/smdi copolymer
dimethicone
cetearyl alcohol
tocopheryl acetate
lavandula angustifolia (lavender) oil
PEG-100 stearate
ceteareth-20
xanthan gum
polyacrylamide
c13-14 isoparaffin
laureth-7
triethanolamine
tetrasodium edta
propylene glycol
methylparaben
propylparaben
diazolidinyl urea

STOP USE AND ASK A DOCTOR IF EXCESSIVE SKIN IRRITATIONS DEVELOPS OR INCREASES

KEEP OUT OF REACH OF CHILDREN - IF SWALLOWED GET MEDICAL HELP OR CONTACT A POISON CONTROL CENTER RIGHT AWAY

PREGNANCY OR BREAST FEEDING

IF PREGNANT OR BREAST FEEDING ASK A HEALTH PROFESSIONAL BEFORE USE

INDICATIONS AND USAGE

HELPS PREVENT THE DEVELOPMENT OF NEW ACNE BLEMISHES.

PENETRATES PORES TO CLEAR MOST ACNE BLEMISHES.

CLEANSE THE SKIN THOROUGHLY BEFORE APPLYING.

COVER THE ENTIRE EFFECTED AREA 1 TO 3 TIMES DAILY

BECAUSE EXCESSIVE DRYING OF THE SKIN MAY OCCUR STATE WITH 1 APPLICATION DAILY THEN GRADUALLY INCREASE TO 2 OR 3 IF NEEDED OR AS DIRECTED BY YOUR DOCTOR

WARNINGS

FOR EXTERNAL USE ONLY

PURPOSE

HELPS PREVENT THE DEVELOPMENT OF NEW ACNE BLEMISHES.
PENETRATES PORES TO CLEAR MOST ACNE BLEMISHES.

DOSAGE AND ADMINISTRATION

CLEANSE THE SKIN THOROUGHLY BEFORE APPLYING.
COVER THE ENTIRE EFFECTED AREA 1 TO 3 TIMES DAILY
BECAUSE EXCESSIVE DRYING OF THE SKIN MAY OCCUR STATE WITH 1 APPLICATION DAILY THEN GRADUALLY INCREASE TO 2 OR 3 IF NEEDED OR AS DIRECTED BY YOUR DOCTOR